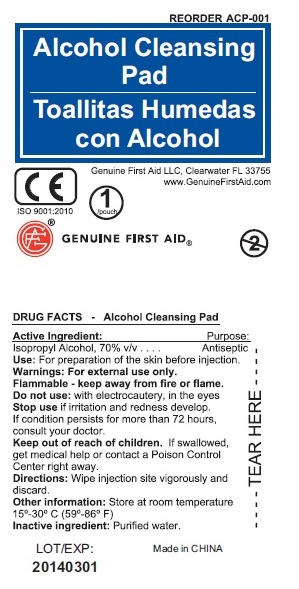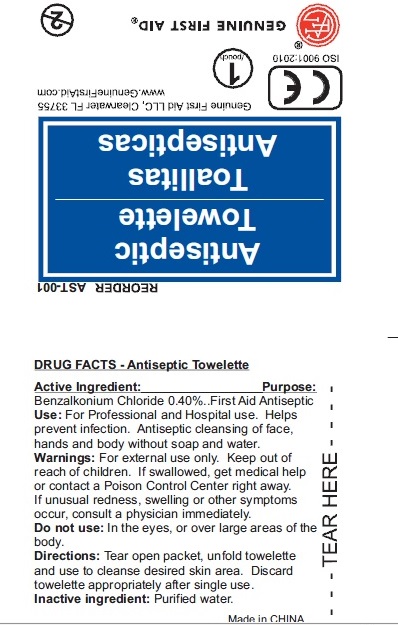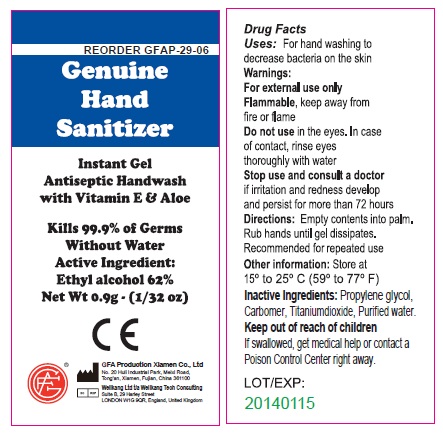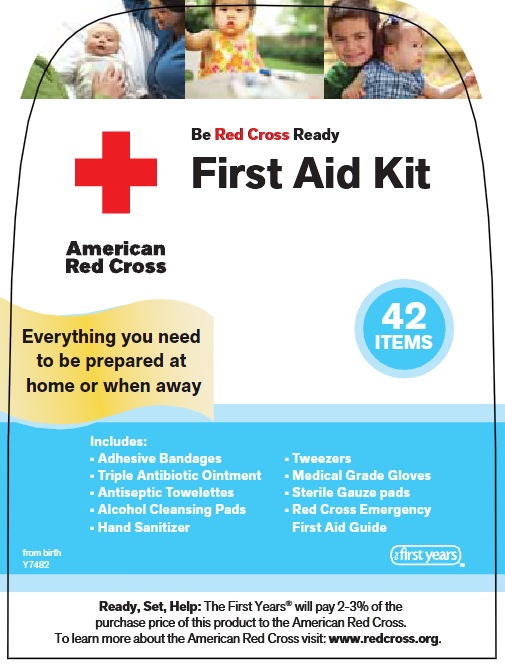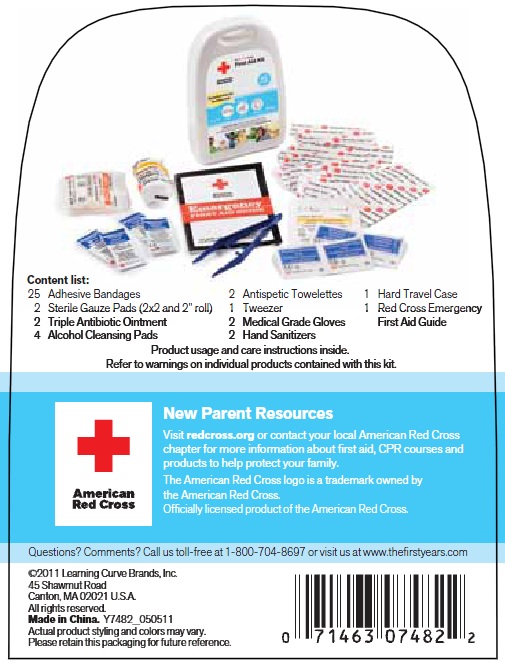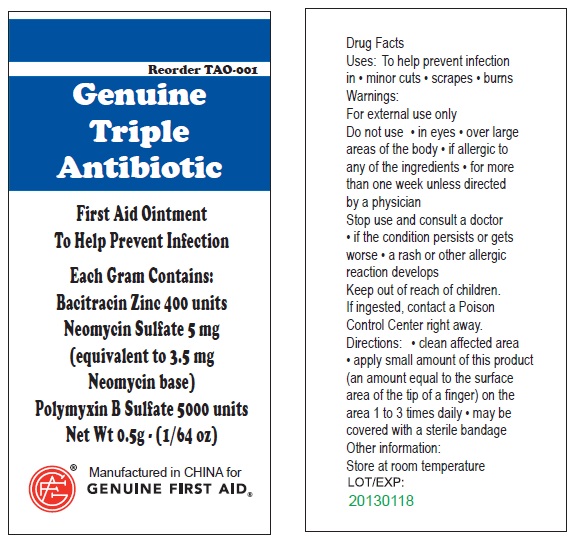 DRUG LABEL: American Red Cross First Aid Kit
NDC: 42354-7482 | Form: KIT | Route: TOPICAL
Manufacturer: Tomy International
Category: otc | Type: HUMAN OTC DRUG LABEL
Date: 20120117

ACTIVE INGREDIENTS: BACITRACIN ZINC 400 [iU]/1 g; NEOMYCIN SULFATE 5 mg/1 g; POLYMYXIN B SULFATE 5000 [iU]/1 g; BENZALKONIUM CHLORIDE 0.40 mL/100 mL; ISOPROPYL ALCOHOL 70 mL/100 mL; ALCOHOL 62 g/100 g
INACTIVE INGREDIENTS: WATER; WATER; WATER; PROPYLENE GLYCOL; TITANIUM DIOXIDE; WATER

Active Ingredient

Isopropyl Alcohol, 70% v/v............... Purpose: Antiseptic

Use

For preparation of skin before injection.

Warnings

For external use only.

STORAGE AND HANDLING

Flammable - keep away from fire or flame
Store at room temperature 15-30 degree Celsius (59-86 degree Fahrenheit)

Do not use:

with electrocautery, in the eyes.

Stop use if irritation and redness develop. If condition persists for more than 72 hours, consult your doctor.

Keep out of reach of children

If swallowed,
get medical help or contact a Poison Control
Center right away.

WHEN USING

Wipe Injection site vigorously and discard.

Inactive Ingredient

Purified water.

DESCRIPTION

LOT/EXP: Made in CHINA
20140301

PACKAGE LABEL

Alcohol Cleansing Pad
Genuine First Aid LLC, Clearwater FL 33755
www.GenuineFirstAid.com
1/pouch
GENUINE FIRST AID

Active Ingredient

Bacitracin Zinc 400 units

Neomycin Sulfate 5mg (equivalent to 3.5 mg Neomycin base)

Polymyxin B Sulfate 5000 units

Uses:

To help prevent infection in:
minor cuts; scrapes; burns

Warnings>

For external use only.

Do not use

in eyes; over large areas of the body;

If allergic to any of the ingredients; for more than one week unless directed by a physician.

Stop use and consult a doctor

if the condition persists or gets worse; a rash or other allergic reaction develops

Keep out of reach of children

If ingested, contact a Poison

Control Center right away.

Directions

Cclean affected area; apply small amount of this product (an amount equal to the surface area of the tip of a finger) on the area 1 to 3 times daily; may be covered with a sterile bandage

Other Information

Store at room temperature.

PACKAGE LABEL

Genuine Triple Antibiotic

First Aid Ointment

To Help Prevent Infection

Each Gram Contains:

Bacitracin Zinc 400 units

Neomycin Sulfate 5 mg

(equivalent to 3.5 mg

Neomycin base)

Polymyxin B Sulfate 5000 units

Net Wt. 0.5g ; (1/64 oz)

Manufactured in CHINA for

GENUINE FIRST AID.

Active Ingredint

Benzalkonium Chloride 0.40%.......... Purpose: First Aid Antiseptic

Use

For Professional and Hospital use. Helps prevent infection. Antiseptic cleansing of face, hands and body without soap and water.

Warning

For external use only.

Keep out of reach of children

If swallowed, get medical help or contact a Poison Control Center right away.

Stop use if unusual redness, swelling or other symptoms occur. Consult a physician immediately.

Do not use in the eyes or over large areas of the body.

WHEN USING

Directions: Tear open packet, unfold towelette and use to cleanse desired skin area. Discard towelette appropriately after single use.

Inactive Ingredient

Purified water

DESCRIPTION

LOT/EXP: Made in CHINA

20130301

Active Ingredient

Ethyl Alcohol 62%

Purpose

Antimicrobial

Uses

For handwashing to decrease bacteria on the skin.

Warnings

For external use only.

Flammable

Do not use

in the eyes. In case of contact, rinse eyes thoroughly with water.

Stop use and consult a doctor

if irritation and redness develop and persist for more than 72 hours

Directions

Empty contents into palm. Rub hands until gel dissipates. Recommended for repeated use.

Inactive Ingredients

Propylene glycol, carbomer, titanium dioxide, purified water

Keep out of reach of children

If swallowed, get medical help or contact a Poison Control Center right away.

PACKAGE LABEL

Genuine Hand Sanitizer

Instant Gel

Antiseptic Handwash with Vitamin E and Aloe

Kills 99.9% of germs without water

Active Ingredient:

Ethyl alcohol 62%

Net Wt 0.9g (1/32oz)

PACKAGE LABEL

Antiseptic Towelette

Genuine First Aid LLC, Clearwater FL 33755

www.GenuineFirstAid.com

1/pouch

GENUINE FIRST AID